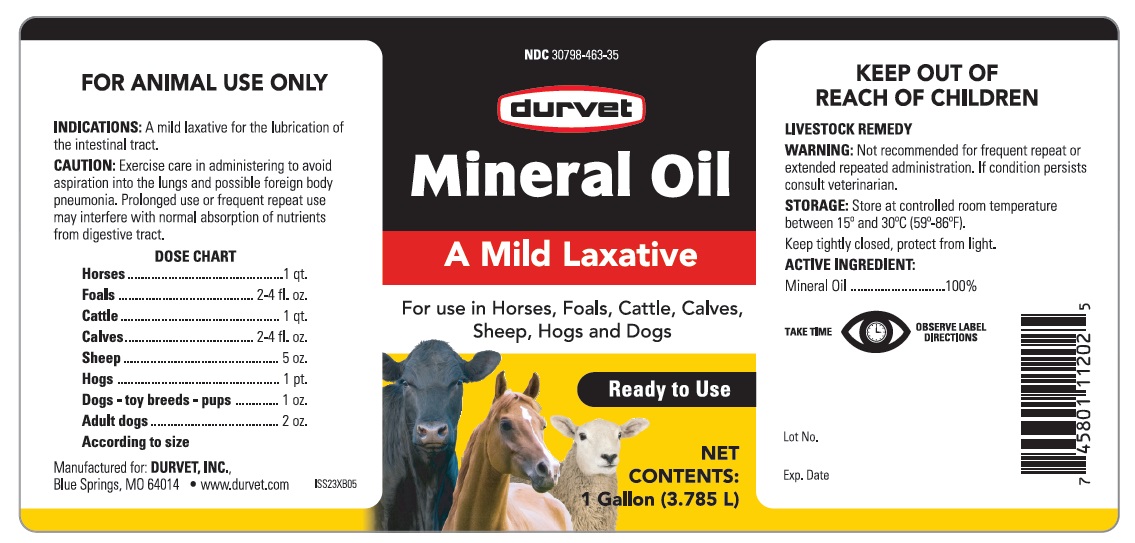 DRUG LABEL: Mineral Oil
NDC: 30798-463 | Form: OIL
Manufacturer: Durvet, Inc.
Category: animal | Type: OTC ANIMAL DRUG LABEL
Date: 20251126

ACTIVE INGREDIENTS: Light Mineral Oil 3.785 L/3.785 L

INDICATIONS AND USAGE

Mineral Oil

A Mild Laxative

For use in Horses, Foals, Cattle, Calves, Sheep, Hogs and Dogs

Ready to Use

Net Contents: 1 Gallon (3.785 L)

FOR ANIMAL USE ONLY

KEEP OUT OF REACH OF CHILDREN

LIVESTOCK REMEDY

INDICATIONS: A mild laxative for the lubrication of the intestinal tract.

CAUTION

Exercise care in administering to avoid aspiration into the lungs and possible foreign body pneumonia. Prolonged use or frequent repeat use may interfere with normal absorption of nutrients from digestive tract.

DOSE CHART

Horse ...................................................... 1 qt.

Foals...................................................... 2-4 fl.oz.

Cattle ...................................................... 1 qt.

Calves ...................................................... 2-4 fl.oz.

Sheep ..................................................... 5 oz.

Hogs ...................................................... 1 pt.

Dogs-toy-breeds-pups ........................ 1 oz.

Adult dogs ............................................ 2 oz.

According to size

WARNING

Not recommended for frequent repeat or extended repeated administration. If condition persists consult veterinarian.

STORAGE

Store at controlled room temperature between 15o and 30oC (59o-86oF). Keep tightly closed, protect from light.

ACTIVE INGREDIENT

Mineral Oil ................................ 100%